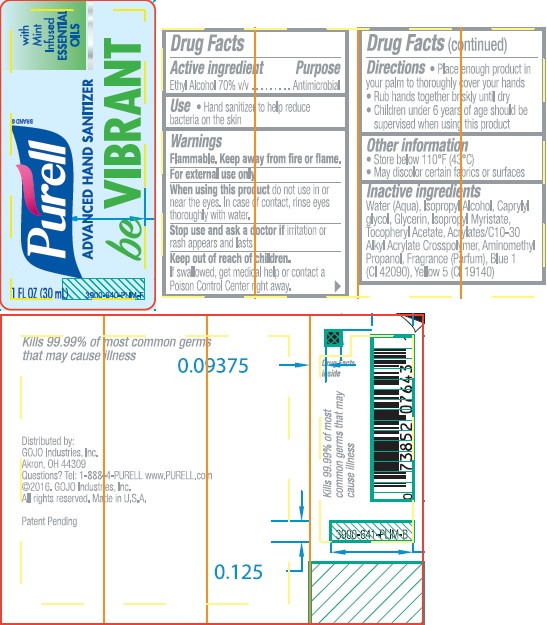 DRUG LABEL: PURELL Advanced Hand Sanitizer be Vibrant
NDC: 21749-028 | Form: GEL
Manufacturer: GOJO Industries, Inc.
Category: otc | Type: HUMAN OTC DRUG LABEL
Date: 20260112

ACTIVE INGREDIENTS: ALCOHOL 0.7 mL/1 mL
INACTIVE INGREDIENTS: WATER; ISOPROPYL ALCOHOL; CAPRYLYL GLYCOL; GLYCERIN; ISOPROPYL MYRISTATE; .ALPHA.-TOCOPHEROL ACETATE; CARBOMER INTERPOLYMER TYPE A (ALLYL SUCROSE CROSSLINKED); AMINOMETHYLPROPANOL; FD&C BLUE NO. 1; FD&C YELLOW NO. 5

PURELL Advanced Hand Sanitizer be Vibrant

Active ingredient

Ethyl alcohol 70% v/v

Purpose

Antimicrobial

Use

Hand sanitizer to help reduce bacteria on the skin

Warnings

Flammable. Keep away from fire or flame. For external use only

When using this product do not use in or near the eyes. In case of contact, rinse eyes thoroughly with water.

Stop use and ask a doctor if irritation or rash appears and lasts

Keep out of reach of children. If swallowed, get medical help or contact a Poison Control Center right away.

Directions

- Place enough product in your palm to thoroughly cover your hands
- Rub hands together briskly until dry
- Children under 6 years of age shodl be supervised when using this product

Other information

• Store below 110°F (43°C)

• May discolor certain fabrics or surfaces

Inactive ingredients

Water (Aqua), Isopropyl Alcohol, Caprylyl glycol, Glycerin, Isopropyl Myristate, Tocopheryl Acetate, Acrylates/C10-30 Alkyl Acrylate Crosspolymer, Aminomethyl Propanol, Fragrance (Parfum), Blue 1 (CI 42090), Yellow 5 (CI 19140)